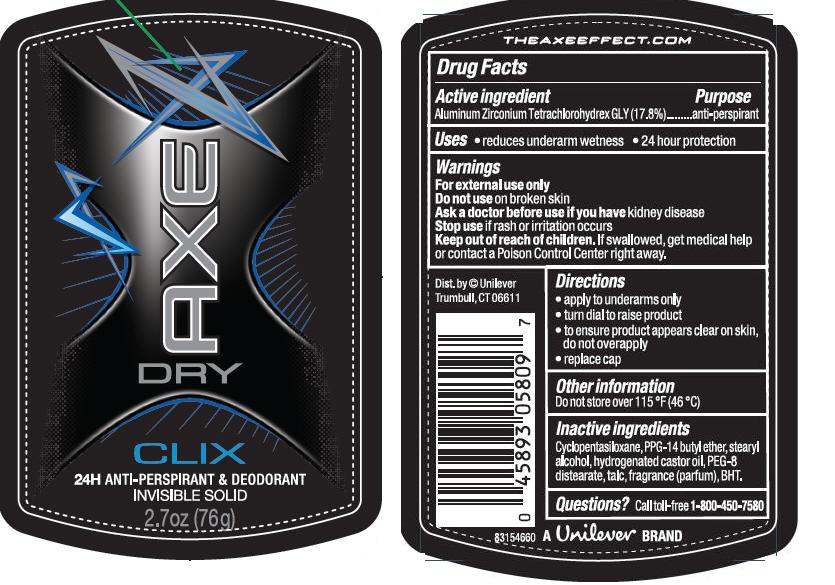 DRUG LABEL: Axe 
NDC: 64942-1152 | Form: STICK
Manufacturer: Conopco Inc. d/b/a Unilever
Category: otc | Type: HUMAN OTC DRUG LABEL
Date: 20101221

ACTIVE INGREDIENTS: Aluminum Zirconium Tetrachlorohydrex GLY 17.8 g/100 g
INACTIVE INGREDIENTS: CYCLOMETHICONE 5; PPG-14 Butyl Ether; Stearyl Alcohol; HYDROGENATED CASTOR OIL; TALC; BUTYLATED HYDROXYTOLUENE

Axe Clix antiperspirant deodorant

Active Ingredient

Aluminum Zirconium Tetrachlorohydrex GLY (17.8%)

Purpose
anti-perspirant

INDICATIONS AND USAGE

Uses · reduces underarm wetness ·24 hour protection

Warnings
For External Use Only

Do not use on broken skin

Ask a doctor before use if you have kidney disease

Stop use if rash or irritation occurs

Keep out of reach of children. If swallowed, get medical help or contact a Poison Control Center right away

Directions
· apply to underarms only
· turn dial to raise product
· to ensure product appears clear on skin, do not overapply
· replace cap

Inactive ingredients
Cyclopentasiloxane
PPG-14 Butyl Ether
Stearyl Alcohol
Hydrogenated Castor Oil
PEG-8 Distearate
Talc
Fragrance (Parfum)
BHT

Questions? Call toll-free 1-800-450-7580

PACKAGE LABEL

PDP 2.7 oz.